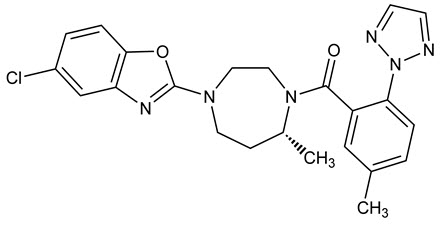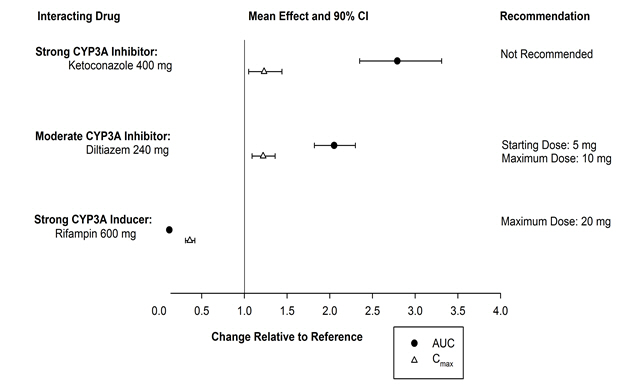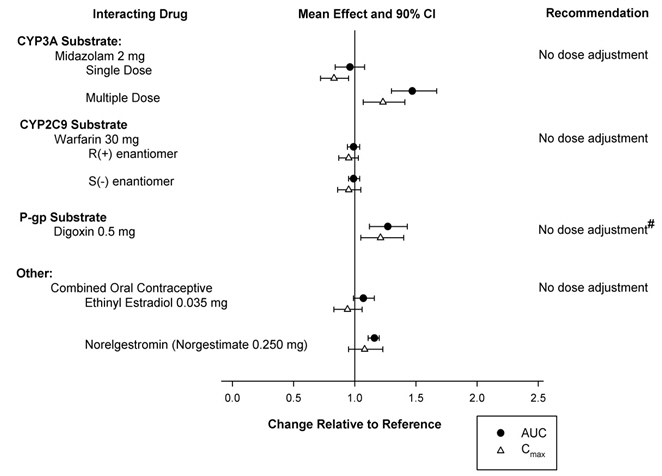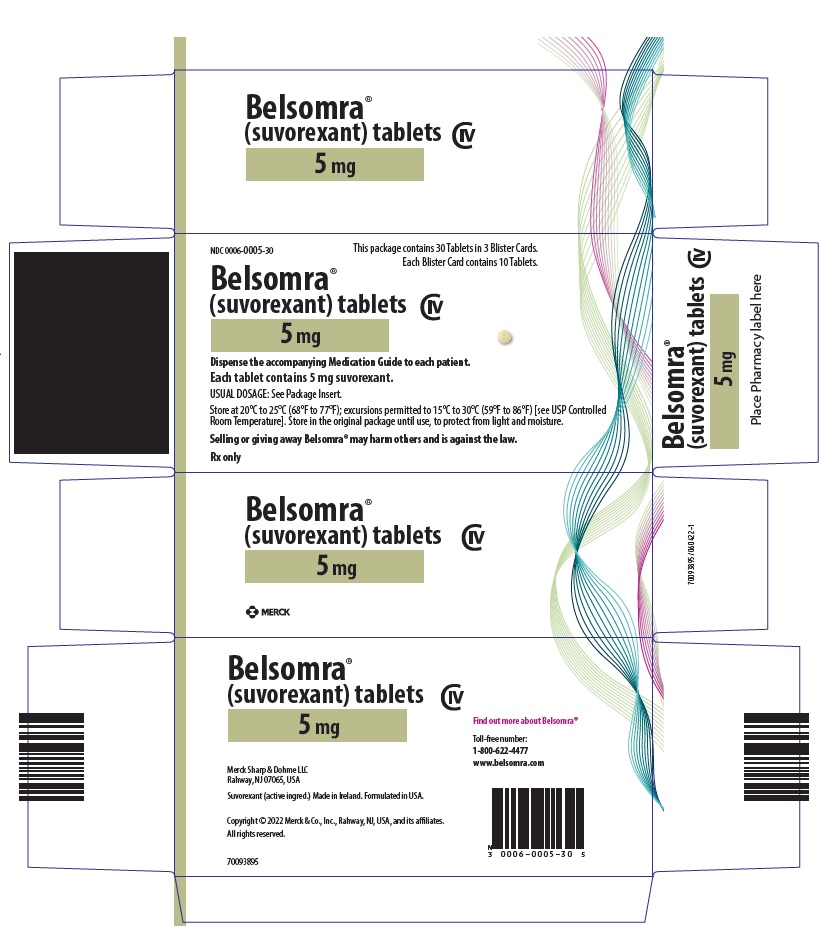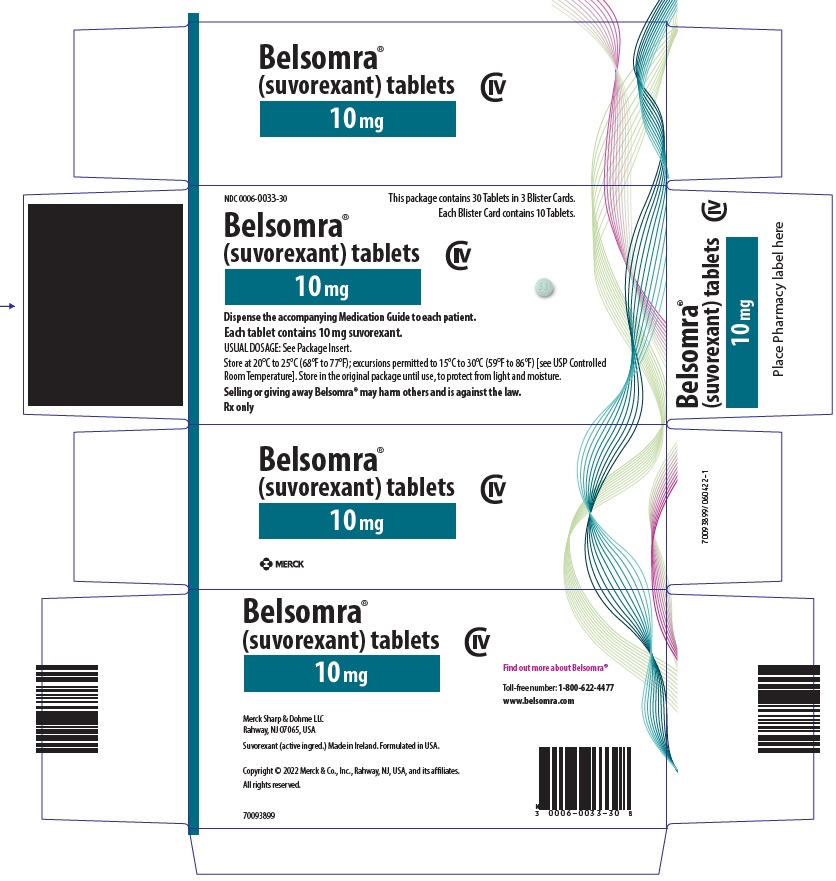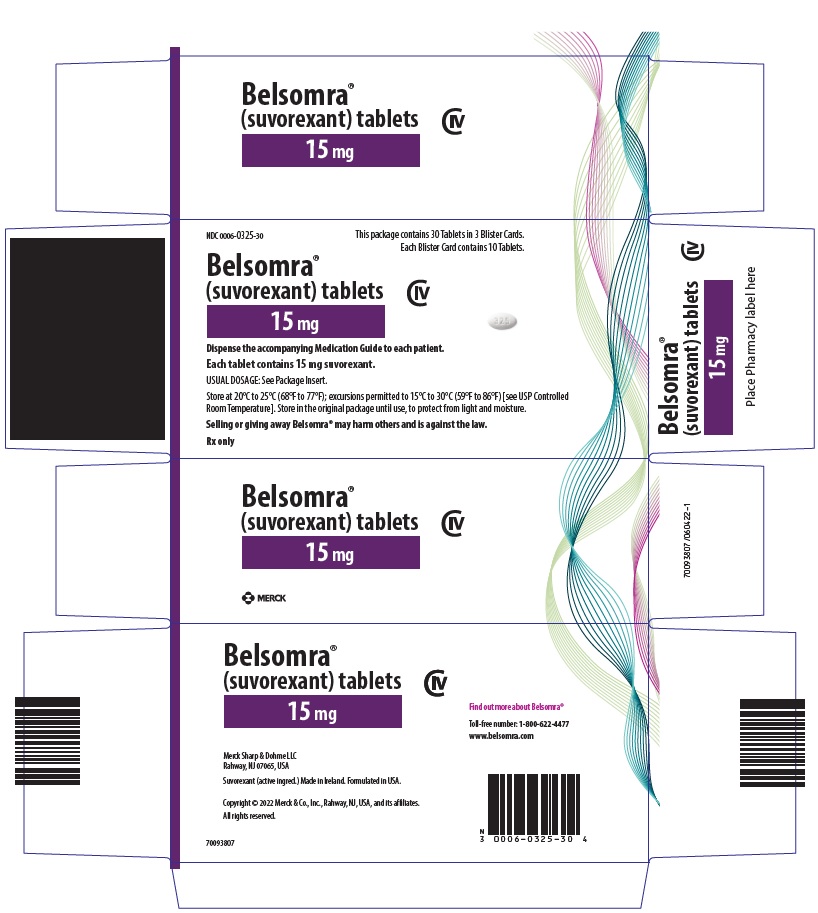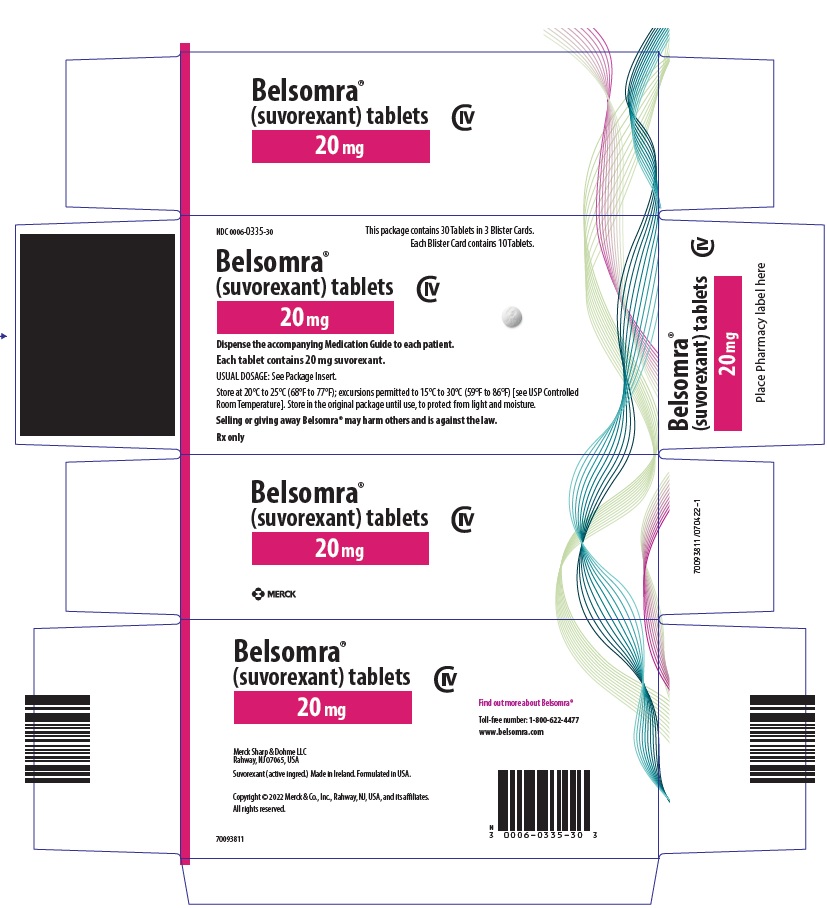 DRUG LABEL: BELSOMRA
NDC: 0006-0005 | Form: TABLET, FILM COATED
Manufacturer: Merck Sharp & Dohme LLC
Category: prescription | Type: HUMAN PRESCRIPTION DRUG LABEL
Date: 20250310
DEA Schedule: CIV

ACTIVE INGREDIENTS: suvorexant 5 mg/1 1
INACTIVE INGREDIENTS: COPOVIDONE K25-31; MICROCRYSTALLINE CELLULOSE; lactose monohydrate; croscarmellose sodium; magnesium stearate; titanium dioxide; triacetin; HYPROMELLOSE, UNSPECIFIED; FERROSOFERRIC OXIDE; FERRIC OXIDE YELLOW

HIGHLIGHTS OF PRESCRIBING INFORMATION

These highlights do not include all the information needed to use BELSOMRA safely and effectively. See full prescribing information for BELSOMRA.
BELSOMRA® (suvorexant) tablets, for oral use, C-IV
Initial U.S. Approval: 2014

1 INDICATIONS AND USAGE

BELSOMRA is an orexin receptor antagonist indicated for the treatment of insomnia, characterized by difficulties with sleep onset and/or sleep maintenance (1).

2 DOSAGE AND ADMINISTRATION

- Use the lowest dose effective for the patient (2.1).
- Recommended dose is 10 mg, no more than once per night taken within 30 minutes of going to bed, with at least 7 hours remaining before the planned time of awakening. If the 10 mg dose is well-tolerated but not effective, the dose can be increased, not to exceed 20 mg once daily (2.1, 2.2).
- Time to effect may be delayed if taken with or soon after a meal (2.1).

3 DOSAGE FORMS AND STRENGTHS

Tablets, 5 mg, 10 mg, 15 mg, 20 mg (3).

4 CONTRAINDICATIONS

BELSOMRA is contraindicated in patients with narcolepsy (4).

5 WARNINGS AND PRECAUTIONS

- CNS Depressant Effects and Daytime Impairment: Risk of impaired alertness and motor coordination, including impaired driving; risk increases with dose; caution patients taking 20 mg against next-day driving and other activities requiring complete mental alertness (5.1).
- Worsening of Depression/Suicidal Ideation: Worsening of depression or suicidal thinking may occur. Risk increases with dose. Immediately evaluate any new behavioral changes (5.2).
- Complex Sleep Behaviors: Behaviors including sleep-walking, sleep-driving, and engaging in other activities while not fully awake may occur. Discontinue immediately if a complex sleep behavior occurs (5.3).
- Sleep Paralysis, Hypnagogic/Hypnopompic Hallucinations, and Cataplexy-like Symptoms: May occur with the use of BELSOMRA. Risk increases with dose (5.4).
- Compromised Respiratory Function: Effect on respiratory function should be considered (5.5, 8.6).
- Need to Evaluate for Co-morbid Diagnoses: Reevaluate if insomnia persists after 7 to 10 days of treatment (5.6).

6 ADVERSE REACTIONS

The most common adverse reaction (reported in 5% or more of patients treated with BELSOMRA and at least twice the placebo rate) with BELSOMRA was somnolence (6.1).

To report SUSPECTED ADVERSE REACTIONS, contact Merck Sharp & Dohme LLC at 1-877-888-4231 or FDA at 1-800-FDA-1088 or www.fda.gov/medwatch.

7 DRUG INTERACTIONS

- CYP3A inhibitors: Recommended dose is 5 mg when used with moderate CYP3A inhibitors. Dose can be increased to 10 mg once per night if the 5 mg dose is not effective. Not recommended for use in patients taking strong CYP3A inhibitors (2.4, 7.2).
- Strong CYP3A inducers: Efficacy may be reduced (7.2).
- Digoxin: Monitor digoxin concentrations (7.3).

8 USE IN SPECIFIC POPULATIONS

Patients with severe hepatic impairment: Not recommended (8.7).

FULL PRESCRIBING INFORMATION

1 INDICATIONS AND USAGE

BELSOMRA® (suvorexant) is indicated for the treatment of insomnia characterized by difficulties with sleep onset and/or sleep maintenance.

2 DOSAGE AND ADMINISTRATION

2.1 Dosing Information

Use the lowest dose effective for the patient. For all BELSOMRA doses, take no more than once per night within 30 minutes of going to bed (with at least 7 hours remaining prior to planned awakening). Time to effect of BELSOMRA may be delayed if taken with or soon after a meal [see Clinical Pharmacology (12.3)].

The recommended dose for BELSOMRA is 10 mg, taken no more than once per night. If the 10 mg dose is well-tolerated but not effective, the dose can be increased. The maximum recommended dose of BELSOMRA is 20 mg taken no more than once per night.

2.2 Special Populations

Exposure to BELSOMRA is increased in obese compared to non-obese patients, and in women compared to men. Particularly in obese women, the increased risk of exposure-related adverse effects should be considered before increasing the dose [see Clinical Pharmacology (12.3)].

2.3 Use with CNS Depressants

When BELSOMRA is combined with other CNS depressant drugs, dosage reduction of BELSOMRA and/or the other drug(s) may be necessary because of potentially additive effects [see Warnings and Precautions (5.1)].

2.4 Dosage Adjustments with CYP3A Inhibitors

When used with moderate CYP3A inhibitors, the recommended dosage of BELSOMRA is 5 mg taken no more than once per night (the dose generally should not exceed 10 mg). BELSOMRA is not recommended for use with strong CYP3A inhibitors [see Drug Interactions (7.2)].

3 DOSAGE FORMS AND STRENGTHS

- 5 mg tablets are yellow, round, film-coated tablets with "5" on one side and plain on the other side.
- 10 mg tablets are green, round, film-coated tablets with "33" on one side and plain on the other side.
- 15 mg tablets are white, oval, film-coated tablets with the corporate logo on one side and "325" on the other side.
- 20 mg tablets are white, round, film-coated tablets with the corporate logo and "335" on one side and plain on the other side.

4 CONTRAINDICATIONS

BELSOMRA is contraindicated in patients with narcolepsy.

5 WARNINGS AND PRECAUTIONS

5.1 CNS Depressant Effects and Daytime Impairment

BELSOMRA is a central nervous system (CNS) depressant that can impair daytime wakefulness even when used as prescribed. Prescribers should monitor for somnolence and CNS depressant effects, but impairment can occur in the absence of symptoms, and may not be reliably detected by ordinary clinical exam (i.e., less than formal testing of daytime wakefulness and/or psychomotor performance). CNS depressant effects may persist in some patients for up to several days after discontinuing BELSOMRA.

BELSOMRA can impair driving skills and may increase the risk of falling asleep while driving. Discontinue or decrease the dose in patients who drive if daytime somnolence develops. In a study of healthy adults, driving ability was impaired in some individuals taking 20 mg BELSOMRA [see Clinical Studies (14.2)]. Although pharmacodynamic tolerance or adaptation to some adverse depressant effects of BELSOMRA may develop with daily use, patients using the 20 mg dose of BELSOMRA should be cautioned against next-day driving and other activities requiring full mental alertness. Patients taking lower doses of BELSOMRA should also be cautioned about the potential for driving impairment because there is individual variation in sensitivity to BELSOMRA.

Co-administration with other CNS depressants (e.g., benzodiazepines, opioids, tricyclic antidepressants, alcohol) increases the risk of CNS depression. Patients should be advised not to consume alcohol in combination with BELSOMRA because of additive effects [see Drug Interactions (7.1)]. Dosage adjustments of BELSOMRA and of concomitant CNS depressants may be necessary when administered together because of potentially additive effects. The use of BELSOMRA with other drugs to treat insomnia is not recommended [see Dosage and Administration (2.3)].

The risk of next-day impairment, including impaired driving, is increased if BELSOMRA is taken with less than a full night of sleep remaining, if a higher than the recommended dose is taken, if co-administered with other CNS depressants, or if co-administered with other drugs that increase blood levels of BELSOMRA. Patients should be cautioned against driving and other activities requiring complete mental alertness if BELSOMRA is taken in these circumstances.

Because BELSOMRA can cause drowsiness, patients, particularly the elderly, are at higher risk of falls.

5.2 Worsening of Depression/Suicidal Ideation

In clinical studies, a dose-dependent increase in suicidal ideation was observed in patients taking BELSOMRA as assessed by questionnaire. Immediately evaluate patients with suicidal ideation or any new behavioral sign or symptom.

In primarily depressed patients treated with sedative-hypnotics, worsening of depression, and suicidal thoughts and actions (including completed suicides) have been reported. Suicidal tendencies may be present in such patients and protective measures may be required. Intentional overdose is more common in this group of patients; therefore, the lowest number of tablets that is feasible should be prescribed for the patient at any one time.

The emergence of any new behavioral sign or symptom of concern requires careful and immediate evaluation.

5.3 Complex Sleep Behaviors

Complex sleep behaviors, including sleep-walking, sleep-driving, and engaging in other activities while not fully awake (e.g., preparing and eating food, making phone calls, having sex), have been reported to occur with the use of hypnotics such as BELSOMRA. These events can occur in hypnotic-naïve as well as in hypnotic-experienced persons. Patients usually do not remember these events. Complex sleep behaviors may occur following the first or any subsequent use of BELSOMRA, with or without the concomitant use of alcohol and other CNS depressants [see Drug Interactions (7.1)]. Discontinue BELSOMRA immediately if a patient experiences a complex sleep behavior.

5.4 Sleep Paralysis, Hypnagogic/Hypnopompic Hallucinations, Cataplexy-Like Symptoms

Sleep paralysis, an inability to move or speak for up to several minutes during sleep-wake transitions, and hypnagogic/hypnopompic hallucinations, including vivid and disturbing perceptions by the patient, can occur with the use of BELSOMRA. Prescribers should explain the nature of these events to patients when prescribing BELSOMRA.

Symptoms similar to mild cataplexy can occur, with risk increasing with the dose of BELSOMRA. Such symptoms can include periods of leg weakness lasting from seconds to a few minutes, can occur both at night and during the day, and may not be associated with an identified triggering event (e.g., laughter or surprise).

5.5 Patients with Compromised Respiratory Function

Effect of BELSOMRA on respiratory function should be considered if prescribed to patients with compromised respiratory function. BELSOMRA has not been studied in patients with severe obstructive sleep apnea (OSA) or severe chronic obstructive pulmonary disease (COPD) [see Use in Specific Populations (8.6)].

5.6 Need to Evaluate for Co-morbid Diagnoses

Because sleep disturbances may be the presenting manifestation of a physical and/or psychiatric disorder, treatment of insomnia should be initiated only after careful evaluation of the patient. The failure of insomnia to remit after 7 to 10 days of treatment may indicate the presence of a primary psychiatric and/or medical illness that should be evaluated. Worsening of insomnia or the emergence of new cognitive or behavioral abnormalities may be the result of an unrecognized underlying psychiatric or physical disorder and can emerge during the course of treatment with hypnotic drugs such as BELSOMRA.

6 ADVERSE REACTIONS

The following serious adverse reactions are discussed in greater detail in other sections:

- CNS Depressant Effects and Daytime Impairment [see Warnings and Precautions (5.1)]
- Worsening of Depression/Suicidal Ideation [see Warnings and Precautions (5.2)]
- Complex Sleep Behaviors [see Warnings and Precautions (5.3)]
- Sleep Paralysis, Hypnagogic/Hypnopompic Hallucinations, Cataplexy-Like Symptoms [see Warnings and Precautions (5.4)]
- Patients with Compromised Respiratory Function [see Warnings and Precautions (5.5)]

6.1 Clinical Trials Experience

Because clinical trials are conducted under widely varying conditions, adverse reaction rates observed in the clinical trials of a drug cannot be directly compared to rates in the clinical trials of another drug and may not reflect the rates observed in clinical practice.

In 3-month controlled efficacy trials (Study 1 and Study 2), 1263 patients were exposed to BELSOMRA including 493 patients who received BELSOMRA 15 mg or 20 mg (see Table 1).

In a long-term study, additional patients (n=521) were treated with BELSOMRA at higher than recommended doses, including a total of 160 patients who received BELSOMRA for at least one year.

Table 1: Patient Exposure to BELSOMRA 15 mg or 20 mg in Study 1 and Study 2
Patients Treated | BELSOMRA 15 mg | BELSOMRA 20 mg
For ≥ 1 Day (n) | 202 | 291
Men (n) | 69 | 105
Women (n) | 133 | 186
Mean Age (years) | 70 | 45
For ≥ 3 Months (n) | 118 | 172

The pooled safety data described below (see Table 2) reflect the adverse reaction profile during the first 3 months of treatment.

Adverse Reactions Resulting in Discontinuation of Treatment

The incidence of discontinuation due to adverse reactions for patients treated with 15 mg or 20 mg of BELSOMRA was 3% compared to 5% for placebo. No individual adverse reaction led to discontinuation at an incidence ≥1%.

Most Common Adverse Reactions

In clinical trials of patients with insomnia treated with BELSOMRA 15 mg or 20 mg, the most common adverse reaction (reported in 5% or more of patients treated with BELSOMRA and at least twice the placebo rate) was somnolence (BELSOMRA 7%; placebo 3%).

Table 2 shows the percentage of patients with adverse reactions during the first three months of treatment, based on the pooled data from 3-month controlled efficacy trials (Study 1 and Study 2).

At doses of 15 or 20 mg, the incidence of somnolence was higher in females (8%) than in males (3%). Of the adverse reactions reported in Table 2, the following occurred in women at an incidence of at least twice that in men: headache, abnormal dreams, dry mouth, cough, and upper respiratory tract infection.

The adverse reaction profile in elderly patients was generally consistent with non-elderly patients. The adverse reactions reported during long-term treatment up to 1 year were generally consistent with those observed during the first 3 months of treatment.

Table 2: Percentage of Patients with Adverse Reactions Incidence ≥2% and Greater than Placebo in 3-Month Controlled Efficacy Trials (Study 1 and Study 2)
 | Placebo | BELSOMRA (20 mg in non-elderly or 15 mg in elderly patients)
 | n=767 | n=493
Gastrointestinal Disorders
Diarrhea | 1 | 2
Dry mouth | 1 | 2
Infections and Infestations
Upper respiratory tract infection | 1 | 2
Nervous System Disorders
Headache | 6 | 7
Somnolence | 3 | 7
Dizziness | 2 | 3
Psychiatric Disorders
Abnormal dreams | 1 | 2
Respiratory, Thoracic and Mediastinal Disorders
Cough | 1 | 2

Dose Relationship for Adverse Reactions

There is evidence of a dose relationship for many of the adverse reactions associated with BELSOMRA use, particularly for certain CNS adverse reactions.

In a placebo-controlled crossover study (Study 3), non-elderly adult patients were treated for up to one month with BELSOMRA at doses of 10 mg, 20 mg, 40 mg (2 times the maximum recommended dose) or 80 mg (4 times the maximum recommended dose). In patients treated with BELSOMRA 10 mg (n=62), the types of adverse reactions observed were similar to those observed in patients treated with BELSOMRA 20 mg. BELSOMRA was associated with a dose-related increase in somnolence: 2% at the 10 mg dose, 5% at the 20 mg dose, 12% at the 40 mg dose, and 11% at the 80 mg dose, compared to <1% for placebo. BELSOMRA was also associated with a dose-related increase in serum cholesterol: 1 mg/dL at the 10 mg dose, 2 mg/dL at the 20 mg dose, 3 mg/dL at the 40 mg dose, and 6 mg/dL at the 80 mg dose after 4 weeks of treatment, compared to a 4 mg/dL decrease for placebo.

Insomnia Study in Patients with Mild to Moderate Alzheimer's Disease

In a 4-week insomnia study of BELSOMRA in 285 patients (BELSOMRA n=142; placebo n=143) with mild to moderate Alzheimer's Disease, the adverse reactions occurring ≥2% and greater than placebo were somnolence (4% compared to 1% for placebo), dry mouth (2% compared to 1% for placebo), and falls (2% compared to 0% for placebo) [see Clinical Studies (14.1)].

6.2 Post-Marketing Experience

The following adverse reactions have been identified during post-approval use of BELSOMRA. Because these reactions are reported voluntarily from a population of uncertain size, it is not always possible to reliably estimate their frequency or establish a causal relationship to drug exposure.

Cardiac disorders: palpitations, tachycardia
Gastrointestinal disorders: nausea, vomiting
Nervous system disorders: psychomotor hyperactivity
Psychiatric disorders: anxiety
Skin and subcutaneous tissue disorders: pruritus

7 DRUG INTERACTIONS

7.1 CNS-Active Agents

When BELSOMRA was co-administered with alcohol, additive psychomotor impairment was demonstrated. There was no alteration in the pharmacokinetics of BELSOMRA [see Warnings and Precautions (5.1, 5.3) and Clinical Pharmacology (12.3)].

7.2 Effects of Other Drugs on BELSOMRA

Metabolism by CYP3A is the major elimination pathway for suvorexant.

CYP3A Inhibitors

Concomitant use of BELSOMRA with strong inhibitors of CYP3A (e.g., ketoconazole, itraconazole, posaconazole, clarithromycin, nefazodone, ritonavir, saquinavir, nelfinavir, indinavir, boceprevir, telaprevir, telithromycin and conivaptan) is not recommended [see Clinical Pharmacology (12.3)].

The recommended dose of BELSOMRA is 5 mg in subjects receiving moderate CYP3A inhibitors (e.g., amprenavir, aprepitant, atazanavir, ciprofloxacin, diltiazem, erythromycin, fluconazole, fosamprenavir, grapefruit juice, imatinib, verapamil). The dose generally should not exceed 10 mg in patients receiving moderate CYP3A inhibitors [see Clinical Pharmacology (12.3)].

CYP3A Inducers

Suvorexant exposure can be substantially decreased when co-administered with strong CYP3A inducers (e.g., rifampin, carbamazepine and phenytoin). The efficacy of BELSOMRA may be reduced [see Clinical Pharmacology (12.3)].

7.3 Effects of BELSOMRA on Other Drugs

Digoxin

Concomitant administration of BELSOMRA with digoxin slightly increased digoxin levels due to inhibition of intestinal P-gp. Digoxin concentrations should be monitored when co-administering BELSOMRA with digoxin [see Clinical Pharmacology (12.3)].

8 USE IN SPECIFIC POPULATIONS

8.1 Pregnancy

Risk Summary

Available data from postmarketing reports with BELSOMRA use in pregnant women are insufficient to establish a drug-associated risk of major birth defects, miscarriage or adverse maternal or fetal outcomes.

In animal reproduction studies, oral administration of suvorexant to pregnant rats and rabbits during the period of organogenesis decreased maternal body weight and/or weight gain at doses ≥ 30 and 28 times the maximum recommended human dose (MRHD) of 20 mg based on AUC in the rat and rabbit, respectively. Suvorexant caused decreased fetal weight at doses ≥ 86 times the MRHD based on AUC in the rat and did not cause significant fetal toxicity at doses up to 28 times the MRHD based on AUC in the rabbit. The no observed adverse effect levels (NOAELs) for fetal toxicity are 25 and 28 times the MRHD based on AUC in the rat and rabbit, respectively. Oral administration of suvorexant to pregnant rats during pregnancy and lactation caused decreased maternal and pup body weight or weight gain at approximately 48 times the MRHD based on AUC. The NOAEL for development toxicity in the rat is 25 times the MRHD based on AUC (see Data).

The estimated background risk of major birth defects and miscarriage for the indicated population is unknown. All pregnancies have a background risk of birth defect, loss, or other adverse outcomes. In the US general population, the estimated background risk of major birth defects and miscarriage in clinically recognized pregnancies is 2 to 4% and 15 to 20%, respectively.

Data

Animal Data

Suvorexant was administered orally to pregnant rats during the period of organogenesis in two separate studies at doses of 30, 150, and 1000 mg/kg/day or 30, 80, and 325 mg/kg/day, which are approximately 3 to 93 times the MRHD based on AUC. Suvorexant decreased maternal weights at doses ≥ 150 mg/kg/day and fetal weights at doses ≥ 325 mg/kg/day. The NOAEL for both maternal and fetal toxicity is 80 mg/kg/day, which is approximately 25 times the MRHD based on AUC.

Suvorexant was administered orally to pregnant rabbits during the period of organogenesis in two separate studies at doses of 40, 100, and 300 mg/kg/day or 50, 150, and 325 mg/kg/day, which are approximately 3 to 70 times the MRHD based on AUC. Suvorexant decreased maternal body weight or weight gain at doses ≥ 150 mg/kg/day. Suvorexant caused excessive maternal toxicity that led to premature deaths at 325 mg/kg/day, which precluded fetal evaluation. Suvorexant did not cause significant fetal toxicity at doses up to 300 mg/kg/day. The NOAELs for maternal and fetal toxicities are 100 mg/kg/day and 300 mg/kg/day, respectively, which are approximately 10 and 28 times the MRHD based on AUC, respectively.

Suvorexant was administered orally to pregnant rats during pregnancy and lactation at doses of 30, 80, and 200 mg/kg/day, which are approximately 8 to 48 times the MRHD based on AUC. Suvorexant caused maternal toxicity of decreased body weight and weight gain and food consumption at 200 mg/kg/day. At this maternally toxic dose, suvorexant caused decreased weight gain in offspring pups. The NOAEL for maternal and developmental toxicity is 80 mg/kg/day, which is approximately 25 times the MRHD based on AUC.

8.2 Lactation

Risk Summary

Suvorexant and its metabolite, hydroxy suvorexant, are present in low concentrations in breast milk with a relative infant dose of less than 1% following maternal oral administration (see Data). There are no data on the effects of suvorexant on the breastfed infant, or the effects on milk production.

The developmental and health benefits of breastfeeding should be considered along with the mother’s clinical need for BELSOMRA and any potential adverse effects on the breastfed infant from BELSOMRA or from the underlying maternal condition.

Data

A single dose (20 mg) milk and plasma lactation study was conducted in 12 healthy lactating women. The mean amount of suvorexant recovered in breast milk was 0.011 mg following a 20 mg maternal dose. The calculated mean daily infant dose was 0.002 mg/kg/day based on the actual infant body weight (i.e., 6.2 kg). The relative infant dose is less than 1% of the maternal dose. Approximately 82% of the amount of suvorexant excreted in breast milk was excreted by 24 hours after a single maternal dose administration.

Suvorexant and its metabolite, hydroxy suvorexant, are present in breast milk and the transfer of hydroxy suvorexant into breast milk is lower than suvorexant (metabolite/parent: 0.13).

8.4 Pediatric Use

Safety and effectiveness in pediatric patients have not been established.

8.5 Geriatric Use

Of the total number of patients treated with BELSOMRA (n=1784) in controlled clinical safety and efficacy studies, 829 patients were 65 years and over, and 159 patients were 75 years and over. No clinically meaningful differences in safety or effectiveness were observed between these patients and younger patients at the recommended doses [see Clinical Pharmacology (12.3) and Clinical Studies (14)].

Because BELSOMRA can increase drowsiness, patients, particularly the elderly, are at a higher risk of falls [see Warnings and Precautions (5.1)].

8.6 Patients with Compromised Respiratory Function

Effects of BELSOMRA on respiratory function should be considered if prescribed to patients with compromised respiratory function.

Obstructive Sleep Apnea

The respiratory depressant effect of BELSOMRA was evaluated after one night and after four consecutive nights of treatment in a randomized, placebo-controlled, 2-period crossover study in patients (n=26) with mild to moderate obstructive sleep apnea. Following once-daily doses of 40 mg, the mean Apnea/Hypopnea Index treatment difference (suvorexant – placebo) on Day 4 was 2.7 (90% CI: 0.22 to 5.09), but there was wide inter- and intra-individual variability such that clinically meaningful respiratory effects of BELSOMRA in obstructive sleep apnea cannot be excluded. BELSOMRA has not been studied in patients with severe obstructive sleep apnea [see Warnings and Precautions (5.5)].

Chronic Obstructive Pulmonary Disease

The respiratory depressant effect of BELSOMRA was evaluated after one night and after four consecutive nights of treatment in a randomized, placebo-controlled, 2-period crossover study in patients (n=25) with mild to moderate chronic obstructive pulmonary disease (COPD). BELSOMRA (40 mg in non-elderly, 30 mg in elderly) had no respiratory depressant effects in patients with mild to moderate COPD, as measured by oxygen saturation. There was wide inter- and intra-individual variability such that clinically meaningful respiratory effects of BELSOMRA in COPD cannot be excluded. BELSOMRA has not been studied in patients with severe COPD [see Warnings and Precautions (5.5)].

8.7 Patients with Hepatic Impairment

No dose adjustment is required in patients with mild and moderate hepatic impairment. BELSOMRA has not been studied in patients with severe hepatic impairment and is not recommended for these patients [see Clinical Pharmacology (12.3)].

8.8 Patients with Renal Impairment

No dose adjustment is required in patients with renal impairment [see Clinical Pharmacology (12.3)].

9 DRUG ABUSE AND DEPENDENCE

9.1 Controlled Substance

BELSOMRA contains suvorexant, a Schedule IV controlled substance.

9.2 Abuse

Abuse of BELSOMRA poses an increased risk of somnolence, daytime sleepiness, impaired reaction time and impaired driving skills [see Warnings and Precautions (5.1)]. Patients at risk for abuse may include those with prolonged use of BELSOMRA, those with a history of drug abuse, and those who use BELSOMRA in combination with alcohol or other abused drugs.

Drug abuse is the intentional non-therapeutic use of a drug, even once, for its desirable psychological or physiological effects. Drug addiction is a cluster of behavioral, cognitive, and physiological phenomena that may include a strong desire to take the drug, difficulties in controlling drug use (e.g., continuing drug use despite harmful consequences, giving a higher priority to drug use than to other activities and obligations), and possible tolerance or physical dependence.

In an abuse liability study conducted in recreational polydrug users (n=36), suvorexant (40, 80 and 150 mg) produced similar effects as zolpidem (15, 30 mg) on subjective ratings of "drug liking" and other measures of subjective drug effects. Because individuals with a history of abuse or addiction to alcohol or other drugs may be at increased risk for abuse and addiction to BELSOMRA, follow such patients carefully.

9.3 Dependence

Physical dependence is a state that develops as a result of physiological adaptation in response to repeated drug use, manifested by withdrawal signs and symptoms after abrupt discontinuation or a significant dose reduction of a drug. In completed clinical trials with BELSOMRA, there was no evidence for physical dependence with the prolonged use of BELSOMRA. There were no reported withdrawal symptoms after discontinuation of BELSOMRA.

10 OVERDOSAGE

There is limited premarketing clinical experience with an overdosage of BELSOMRA. In clinical pharmacology studies, healthy subjects who were administered morning doses of up to 240 mg of suvorexant showed dose-dependent increases in the frequency and duration of somnolence.

General symptomatic and supportive measures should be used, along with immediate gastric lavage where appropriate. Intravenous fluids should be administered as needed. As in all cases of drug overdose, vital signs should be monitored and general supportive measures employed. The value of dialysis in the treatment of overdosage has not been determined. As suvorexant is highly protein-bound, hemodialysis is not expected to contribute to elimination of suvorexant.

As with the management of all overdosage, the possibility of multiple drug ingestion should be considered. Consider contacting a poison control center for up-to-date information on the management of hypnotic drug product overdosage.

11 DESCRIPTION

BELSOMRA tablets contain suvorexant, an orexin receptor antagonist.

Suvorexant is described chemically as:

[(7R)-4-(5-chloro-2-benzoxazolyl) hexahydro-7-methyl-1H-1,4-diazepin-1-yl][5-methyl-2-(2H-1,2,3-triazol-2-yl)phenyl]methanone

Its empirical formula is C23H23ClN6O2 and the molecular weight is 450.92. Its structural formula is:

Suvorexant is a white to off-white powder that is insoluble in water.

Each film coated tablet contains 5 mg, 10 mg, 15 mg, or 20 mg of suvorexant and the following inactive ingredients: croscarmellose sodium, lactose monohydrate, magnesium stearate, microcrystalline cellulose, and polyvinylpyrrolidone/vinyl acetate copolymer (copovidone).

In addition, the film coating contains the following inactive ingredients: hypromellose, lactose monohydrate, titanium dioxide, and triacetin. The film coating for the 5 mg tablets also contains iron oxide black and iron oxide yellow, and the film coating for the 10 mg tablets also contains FD&C Blue #1/Brilliant Blue FCF Aluminum Lake and iron oxide yellow.

12 CLINICAL PHARMACOLOGY

12.1 Mechanism of Action

The mechanism of action of suvorexant in the treatment of insomnia is presumed to be through antagonism of orexin receptors. The orexin neuropeptide signaling system plays a role in wakefulness. Blocking the binding of wake-promoting neuropeptides orexin A and orexin B to receptors OX1R and OX2R is thought to suppress wake drive.

12.2 Pharmacodynamics

Suvorexant binds to orexin receptors, OX1R and OX2R (Ki= 0.55 and 0.35 nM, respectively).

Antagonism of orexin receptors may also underlie potential adverse effects such as signs of narcolepsy/cataplexy. Genetic mutations in the orexin system in animals result in hereditary narcolepsy; loss of orexin neurons has been reported in humans with narcolepsy.

Evaluation of QTc Interval

The effects of suvorexant on the QTc interval were evaluated in a randomized, placebo-, and active-controlled (moxifloxacin 400 mg) crossover study in healthy subjects (n=53). The upper bound of the one-sided 95% confidence interval for the largest placebo-adjusted, baseline-corrected QTc interval was below 10 ms based on analysis of suvorexant doses up to 240 mg, 12 times the maximum recommended dose. BELSOMRA thus does not prolong the QTc interval to any clinically relevant extent.

12.3 Pharmacokinetics

Suvorexant exposure increases in a less than strictly dose-proportional manner over the range of 10-80 mg because of decreased absorption at higher doses. Suvorexant pharmacokinetics are similar in healthy subjects and patients with insomnia.

Absorption

Suvorexant peak concentrations occur at a median Tmax of 2 hours (range 30 minutes to 6 hours) under fasted conditions. The mean absolute bioavailability of 10 mg is 82%.

Effect of Food

Ingestion of BELSOMRA with a high-fat meal resulted in no meaningful change in AUC or Cmax but a delay in Tmax of approximately 1.5 hours [see Dosage and Administration (2.1)].

Distribution

The mean volume of distribution of suvorexant is approximately 49 liters. Suvorexant is extensively bound (>99%) to human plasma proteins and does not preferentially distribute into red blood cells. Suvorexant binds to both human serum albumin and α1-acid glycoprotein.

Elimination

Metabolism

Suvorexant is mainly eliminated by metabolism, primarily by CYP3A with a minor contribution from CYP2C19. The major circulating entities are suvorexant and a hydroxy-suvorexant metabolite. This metabolite is not expected to be pharmacologically active.

Excretion

The primary route of elimination is through the feces, with approximately 66% of radiolabeled dose recovered in the feces compared to 23% in the urine. The systemic pharmacokinetics of suvorexant are linear with an accumulation of approximately 1- to 2-fold with once-daily dosing. Steady-state is achieved by 3 days. The mean t1/2 is approximately 12 hours (95% CI: 12 to 13).

Specific Populations

Gender, age, body mass index (BMI), and race were included as factors assessed in the population pharmacokinetic model to evaluate suvorexant pharmacokinetics in healthy subjects and to predict exposures in the patient population. Age and race are not predicted to have any clinically meaningful changes on suvorexant pharmacokinetics; therefore, no dose adjustment is warranted based upon these factors.

Suvorexant exposure is higher in females than in males. In females, the AUC and Cmax are increased by 17% and 9%, respectively, following administration of BELSOMRA 40 mg. The average concentration of suvorexant 9 hours after dosing is 5% higher for females across the dose range studied (10-40 mg). Dose adjustment of BELSOMRA is generally not needed based on gender only.

Apparent oral clearance of suvorexant is inversely related to body mass index. In obese patients, the AUC and Cmax are increased by 31% and 17%, respectively. The average concentration of suvorexant approximately 9 hours after a 20 mg dose is 15% higher in obese patients (BMI > 30 kg/m^2) relative to those with a normal BMI (BMI ≤ 25 kg/m^2).

In obese females, the AUC and Cmax are increased by 46% and 25%, respectively, compared to non-obese females. The higher exposure to suvorexant in obese females should be considered before increasing dose [see Dosage and Administration (2.2)].

The effects of renal and hepatic impairment on the pharmacokinetics of suvorexant were evaluated in specific pharmacokinetic studies.

Suvorexant exposure after a single dose was similar in patients with moderate hepatic insufficiency (Child-Pugh category 7 to 9) and healthy matched control subjects; however, the suvorexant apparent terminal half-life was increased from approximately 15 hours (range 10 - 22 hours) in healthy subjects to approximately 19 hours (range 11 - 49 hours) in patients with moderate hepatic insufficiency [see Use in Specific Populations (8.7)].

Suvorexant exposure (expressed as total and unbound concentrations) was similar between patients with severe renal impairment (urinary creatinine clearance ≤30 mL/min/1.73m^2) and healthy matched control subjects. No dose adjustment is required in patients with renal impairment [see Use in Specific Populations (8.8)].

Drug Interaction Studies

CNS-Active Drugs

An additive effect on psychomotor performance was observed when a single dose of 40 mg of suvorexant was co-administered with a single dose of 0.7 g/kg alcohol. Suvorexant did not affect alcohol concentrations and alcohol did not affect suvorexant concentrations [see Warnings and Precautions (5.1, 5.3) and Drug Interactions (7.1)].

An interaction study with a single dose of 40 mg suvorexant and paroxetine 20 mg at steady-state levels in healthy subjects did not demonstrate a clinically significant pharmacokinetic or pharmacodynamic interaction.

Effects of Other Drugs on BELSOMRA

The effects of other drugs on the pharmacokinetics of suvorexant are presented in Figure 1 as change relative to suvorexant administered alone (test/reference). Strong (e.g., ketoconazole or itraconazole) and moderate (e.g., diltiazem) CYP3A inhibitors significantly increased suvorexant exposure. Strong CYP3A inducers (e.g., rifampin) substantially decreased suvorexant exposure [see Drug Interactions (7.2)].

Figure 1: Effects of Co-Administered Drugs on the Pharmacokinetics of Suvorexant

Effects of BELSOMRA on Other Drugs

In vitro metabolism studies demonstrate that suvorexant has the potential to inhibit CYP3A and intestinal P-gp; however, suvorexant is unlikely to cause clinically significant inhibition of human CYP1A2, CYP2B6, CYP2C8, CYP2C9, CYP2C19 or CYP2D6. In addition, no clinically meaningful inhibition of OATP1B1, BCRP and OCT2 transporters is anticipated. Chronic administration of suvorexant is unlikely to induce the metabolism of drugs metabolized by major CYP isoforms. Specific in vivo effects on the pharmacokinetics of midazolam, warfarin, digoxin and oral contraceptives are presented in Figure 2 as a change relative to the interacting drug administered alone (test/reference) [see Drug Interactions (7.3)].

Figure 2: Effects of Suvorexant [Suvorexant 40 mg was evaluated in all studies, except midazolam where 80 mg suvorexant was administered.] on the Pharmacokinetics of Co-Administered Drugs

# Monitor digoxin concentrations as clinically indicated [see Drug Interactions (7.3)].

13 NONCLINICAL TOXICOLOGY

13.1 Carcinogenesis, Mutagenesis, Impairment of Fertility

Carcinogenesis

Rats were orally administered suvorexant at doses of 80, 160, and 325 mg/kg/day [males] or 40, 80, and 325 mg/kg/day [females] for 2 years. Suvorexant increased the incidences of thyroid follicular cell adenoma and combined adenoma/carcinoma in females at 325 mg/kg/day, thyroid follicular cell adenoma in males at ≥ 160 mg/kg/day, and hepatocellular adenoma in males at 325 mg/kg/day. These findings were consistent with increased TSH and hepatic enzyme induction, respectively, which are mechanisms believed to be rodent-specific. Suvorexant did not increase the incidence of tumors in rats at 80 mg/kg/day, which is approximately 7 times the MRHD based on AUC.

Suvorexant did not increase the incidence of tumors in Tg.rasH2 mice treated for 26 weeks at oral doses of 25, 50, 200, and 650 mg/kg/day.

Mutagenesis

Suvorexant was not mutagenic in the in vitro bacterial reverse mutation (Ames) assay or clastogenic in the in vitro mammalian chromosomal aberration assay or in the in vivo mouse and rat bone marrow micronucleus assays.

Impairment of Fertility

In two separate studies, suvorexant was orally administered to male and female rats at doses of 80, 160, and 325 mg/kg/day or 100, 300, and 1200 mg/kg/day [males] and 30, 80, and 325 mg/kg/day or 25, 75, and 1200 mg/kg/day [females] prior to and throughout mating and continuing in females to gestation day 7. Increases in pre-implantation loss and resorption and decreases in live fetuses were observed at the highest doses of 325 or 1200 mg/kg/day, when treated males and females were mated with untreated animals. The NOAELs for fertility are 160 and 80 mg/kg/day in males and females, respectively, which are approximately 20 times the MRHD based on AUC.

13.2 Animal Toxicology and/or Pharmacology

Suvorexant administered to dogs at oral doses of 5 and 30 mg/kg/day for 4 to 7 days resulted in behaviors characteristic of cataplexy (e.g., transient limb buckling, prone posture) when presented with food enrichment, a stimulus demonstrated to induce cataplexy in dogs with hereditary narcolepsy.

In the 2-year carcinogenicity study in rats, an increased incidence of retinal atrophy was observed at all doses. Plasma AUCs at the lowest dose tested were approximately 7 times that in humans at the MRHD.

In subsequent studies of suvorexant in albino and pigmented rats, retinal atrophy was delayed in onset and, after approximately one year of dosing, was of lower incidence and severity in pigmented rats.

14 CLINICAL STUDIES

14.1 Controlled Clinical Studies

BELSOMRA was evaluated in three clinical trials in patients with insomnia characterized by difficulties with sleep onset and sleep maintenance.

Two similarly designed, 3-month, randomized, double-blind, placebo-controlled, parallel-group studies were conducted (Study 1 and Study 2). In both studies, non-elderly (age 18-64) and elderly (age ≥ 65) patients were randomized separately. For the studies together, non-elderly adults (mean age 46 years; 465 females, 275 males) were treated with BELSOMRA 20 mg (n=291) or placebo (n=449). Elderly patients (mean age 71 years, 346 females, 174 males) were treated with BELSOMRA 15 mg (n=202) or placebo (n=318).

In Study 1 and Study 2, BELSOMRA 15 mg or 20 mg was superior to placebo for sleep latency as assessed both objectively by polysomnography (Table 3) and subjectively by patient-estimated sleep latency (Table 4). BELSOMRA 15 mg or 20 mg was also superior to placebo for sleep maintenance, as assessed both objectively by polysomnography (Table 5) and subjectively by patient-estimated total sleep time (Table 6). The effects of BELSOMRA at night 1 (objective) and week 1 (subjective) were generally consistent with later time points. The efficacy of BELSOMRA was similar between women and men and, based on limited data, between Caucasians and non-Caucasians. Twenty seven percent of patients treated with BELSOMRA 15 mg or 20 mg in Study 1 and Study 2 were non-Caucasians. The majority (69%) of the non-Caucasian patients was Asian.

Table 3: Polysomnographic Assessment of Time to Sleep Onset in Studies 1 and 2
 | Mean Baseline and Change from Baseline† After 1 and 3 Months (minutes) |  | Difference† Between BELSOMRA and Placebo (minutes)
Study 1
 | Placebo (n=290) | BELSOMRA 15-20 mg‡ (n=193)
Baseline | 66 | 69
Change from Baseline
Month 1 | - 23 | - 34 | - 10***
Month 3 | - 27 | - 35 | - 8**
Study 2
 | Placebo (n=286) | BELSOMRA 15-20 mg‡ (n=145)
Baseline | 69 | 65
Change from Baseline
Month 1 | - 25 | - 33 | - 8*
Month 3 | - 29 | - 29 | 0
† Change from baseline and treatment differences based upon estimated means.
‡ 15 mg in elderly and 20 mg in non-elderly patients
* p<0.05; **p<0.01; ***p<0.001

Table 4: Patient-Estimated Time to Sleep Onset in Studies 1 and 2
 | Mean Baseline and Change from Baseline† After 1 and 3 Months (minutes) |  | Difference† Between BELSOMRA and Placebo (minutes)
Study 1
 | Placebo (n=382) | BELSOMRA 15-20 mg‡ (n=251)
Baseline | 67 | 64
Change from Baseline
Month 1 | - 12 | - 17 | - 5
Month 3 | - 17 | - 23 | - 5*
Study 2
 | Placebo (n=369) | BELSOMRA 15-20 mg‡ (n=231)
Baseline | 83 | 86
Change from Baseline
Month 1 | - 14 | - 21 | - 7*
Month 3 | - 21 | - 28 | - 8*
† Change from baseline and treatment differences based upon estimated means.
‡ 15 mg in elderly and 20 mg in non-elderly patients
* p<0.05; **p<0.01; ***p<0.001

Table 5: Polysomnographic Assessment of Sleep Maintenance (Wake After Sleep Onset) in Studies 1 and 2
 | Mean Baseline and Change from Baseline† After 1 and 3 Months (minutes) |  | Difference† Between BELSOMRA and Placebo (minutes)
Study 1
 | Placebo (n=290) | BELSOMRA 15-20 mg‡ (n=193)
Baseline | 115 | 120
Change from Baseline
Month 1 | - 19 | - 45 | - 26***
Month 3 | - 25 | - 42 | - 17***
Study 2
 | Placebo (n=286) | BELSOMRA 15-20 mg‡ (n=145)
Baseline | 118 | 119
Change from Baseline
Month 1 | - 23 | - 47 | - 24***
Month 3 | - 25 | - 56 | - 31***
† Change from baseline and treatment differences based upon estimated means.
‡ 15 mg in elderly and 20 mg in non-elderly patients
* p<0.05; **p<0.01; ***p<0.001

Table 6: Patient-Estimated Total Sleep Time in Studies 1 and 2
 | Mean Baseline and Change from Baseline† After 1 and 3 Months (minutes) |  | Difference† Between BELSOMRA and Placebo (minutes)
Study 1
 | Placebo (n=382) | BELSOMRA 15-20 mg‡ (n=251)
Baseline | 315 | 322
Change from Baseline
Month 1 | 23 | 39 | 16***
Month 3 | 41 | 51 | 11*
Study 2
 | Placebo (n=369) | BELSOMRA 15-20 mg‡ (n=231)
Baseline | 307 | 299
Change from Baseline
Month 1 | 22 | 43 | 21***
Month 3 | 38 | 60 | 22***
† Change from baseline and treatment differences based upon estimated means.
‡ 15 mg in elderly and 20 mg in non-elderly patients
* p<0.05; **p<0.01; ***p<0.001

In the 1-month crossover study (Study 3), non-elderly adults (age 18-64 years, mean age 44 years) were treated with placebo (n=249) and BELSOMRA at a dose of 10 mg (n=62), 20 mg (n=61), or up to 80 mg. BELSOMRA 10 mg and 20 mg were superior to placebo for sleep latency and sleep maintenance, as assessed objectively by polysomnography.

BELSOMRA was also evaluated at doses of 30 mg and 40 mg in the 3-month placebo-controlled trials (Study 1 and Study 2). The higher doses were found to have similar efficacy to lower doses, but significantly more adverse reactions were reported at the higher doses.

Insomnia Study in Patients with Mild to Moderate Alzheimer's Disease

A randomized, double-blind, placebo-controlled, parallel-group, multi-site 4-week trial of BELSOMRA was conducted in patients with mild to moderate Alzheimer's disease (n=285) for the treatment of insomnia. Male and female subjects aged 50-90 years (inclusive) were treated with BELSOMRA (n=142) or placebo (n=143). Patients treated with BELSOMRA received 10 mg for approximately 14 days, of whom 77% were increased to 20 mg for approximately 14 additional days.

In this study, patients treated with BELSOMRA exhibited a statistically significant improvement for both Total Sleep Time (TST) and Wake After Sleep Onset (WASO) measures, compared to those treated with placebo, as assessed by polysomnography at Week 4.

14.2 Special Safety Studies

Effects on Driving

Two randomized, double-blind, placebo- and active-controlled, four-period crossover studies evaluated the effects of nighttime administration of BELSOMRA on next-morning driving performance 9 hours after dosing in 24 healthy elderly subjects (≥65 years old, mean age 69 years; 14 men, 10 women) who received 15 mg and 30 mg BELSOMRA, and 28 non-elderly subjects (mean age 46 years; 13 men, 15 women) who received 20 mg and 40 mg BELSOMRA. Testing was conducted after one night and after 8 consecutive nights of treatment with BELSOMRA at these doses.

The primary outcome measure was change in Standard Deviation of Lane Position (SDLP), a measure of driving performance, assessed using a symmetry analysis. The analysis showed clinically meaningful impaired driving performance in some subjects. After one night of dosing, this effect was observed in non-elderly subjects after either a 20 mg or 40 mg dose of BELSOMRA. A statistically significant effect was not observed in elderly subjects after a 15 mg or 30 mg dose of BELSOMRA. Across these two studies, five subjects (4 non-elderly women on BELSOMRA; 1 elderly woman on placebo) prematurely stopped their driving tests due to somnolence. Patients using the 20 mg dose of BELSOMRA should be cautioned against next-day driving and other activities requiring full mental alertness. Patients taking lower doses of BELSOMRA should also be cautioned about the potential for driving impairment because there is individual variation in sensitivity to BELSOMRA [see Warnings and Precautions (5.1)].

Effects on Next-Day Memory and Balance in Elderly and Non-Elderly

Four placebo-controlled trials evaluated the effects of nighttime administration of BELSOMRA on next-day memory and balance using word learning tests and body sway tests, respectively. Three trials showed no significant effects on memory or balance compared to placebo. In a fourth trial in healthy non-elderly subjects, there was a significant decrease in word recall after the words were presented to subjects in the morning following a single dose of 40 mg BELSOMRA, and there was a significant increase on body sway area in the morning following a single dose of 20 mg or 40 mg BELSOMRA.

Middle of the Night Safety in Elderly Subjects

A double-blind, randomized, placebo-controlled trial evaluated the effect of a single dose of BELSOMRA on balance, memory and psychomotor performance in healthy elderly subjects (n=12) after being awakened during the night. Nighttime dosing of BELSOMRA 30 mg resulted in impairment of balance (measured by body sway area) at 90 minutes as compared to placebo. Memory was not impaired, as assessed by an immediate and delayed word recall test at 4 hours post-dose.

Rebound Effects

In 3-month controlled safety and efficacy trials (Study 1, Study 2), rebound insomnia was assessed following discontinuation of BELSOMRA relative to placebo and baseline in non-elderly adult patients receiving BELSOMRA 40 mg or 20 mg and in elderly patients receiving BELSOMRA 30 mg or 15 mg. No clear effects were observed on measures of sleep onset or maintenance.

Withdrawal Effects

In 3-month controlled safety and efficacy trials (Study 1, Study 2), withdrawal effects were assessed following discontinuation in non-elderly adult patients who received BELSOMRA 40 mg or 20 mg and elderly patients who received BELSOMRA 30 mg or 15 mg. The analysis showed no clear evidence of withdrawal in the overall study population based on assessment of patient responses to the Tyrer Withdrawal Symptom Questionnaire or assessment of withdrawal-related adverse events following the discontinuation of BELSOMRA.

Respiratory Safety

Use in Healthy Subjects with Normal Respiratory Function

A randomized, placebo-controlled, double-blind, crossover trial in healthy non-elderly subjects (n=12) evaluated the respiratory depressant effect of BELSOMRA (40 mg and 150 mg) after one night of treatment. At the doses studied, BELSOMRA had no respiratory depressant effect as measured by oxygen saturation [see Warnings and Precautions (5.5) and Use in Specific Populations (8.6)].

16 HOW SUPPLIED/STORAGE AND HANDLING

16.1 How Supplied

BELSOMRA tablets, 5 mg, are yellow, round, film-coated tablets, with "5" on one side and plain on the other side. They are supplied as follows: NDC 0006-0005-30 unit-of-use blisters of 30

BELSOMRA tablets, 10 mg, are green, round, film-coated tablets, with "33" on one side and plain on the other side. They are supplied as follows: NDC 0006-0033-30 unit-of-use blisters of 30

BELSOMRA tablets, 15 mg, are white, oval, film-coated tablets with the corporate logo on one side and "325" on the other side. They are supplied as follows: NDC 0006-0325-30 unit-of-use blisters of 30

BELSOMRA tablets, 20 mg, are white, round, film-coated tablets with the corporate logo and "335" on one side and plain on the other side. They are supplied as follows: NDC 0006-0335-30 unit-of-use blisters of 30

16.2 Storage and Handling

Store at 20°C to 25°C (68°F to 77°F); excursions permitted to 15°C to 30°C (59°F to 86°F), [see USP Controlled Room Temperature]. Store in the original package until use to protect from light and moisture.

17 PATIENT COUNSELING INFORMATION

Advise the patient to read the FDA-approved patient labeling (Medication Guide).

CNS Depressant Effects and Next-Day Impairment

Tell patients that BELSOMRA has the potential to cause next-day impairment, and that this risk is increased with higher doses or if dosing instructions are not carefully followed. Patients using the 20 mg dose should be cautioned against next-day driving and other activities requiring full mental alertness as this dose is associated with a higher risk of impaired driving. Patients taking lower doses should also be cautioned about the potential for driving impairment because there is individual variation in sensitivity to BELSOMRA.

Patients should not drive or engage in other activities requiring full alertness within 8 hours of dosing of BELSOMRA. Advise patients that increased drowsiness may increase the risk of falls in some patients [see Warnings and Precautions (5.1)].

Sleep-Driving and Other Complex Behaviors

Instruct patients to inform their families that BELSOMRA has been associated with getting out of bed while not being fully awake, and tell patients and their families to call their healthcare providers if this occurs.

Hypnotics, like BELSOMRA, have been associated with "sleep-driving" and other complex behaviors while not being fully awake (preparing and eating food, making phone calls, or having sex). Tell patients and their families to call their healthcare providers if they develop any of these symptoms.

Suicide

Tell patients to report any worsening of depression or suicidal thoughts immediately.

Alcohol and Other Drugs

Ask patients about alcohol consumption, prescription medicines they are taking, and drugs they may be taking without a prescription. Advise patients not to use BELSOMRA if they drank alcohol that evening or before bed.

Tolerance, Abuse, and Dependence

Tell patients not to increase the dose of BELSOMRA on their own, and to inform you if they believe the drug "does not work."

Administration Instructions

Advise patients to take BELSOMRA only when preparing for or getting into bed and only if they can stay in bed for a full night before being active again. Advise patients to report all of their prescription and nonprescription medicines, vitamins and herbal supplements to the prescriber.

Distributed By: Merck Sharp & Dohme LLC
Rahway, NJ 07065, USA

For patent information: www.msd.com/research/patent

Copyright © 2014-2025 Merck & Co., Inc., Rahway, NJ, USA, and its affiliates.
All rights reserved.

uspi-mk4305-t-2503r011

MEDICATION GUIDE
BELSOMRA® (bell-SOM-rah)
suvorexant
Tablets C-IV

What is the most important information I should know about BELSOMRA?
BELSOMRA may cause serious side effects including:

- Decreased awareness and alertness. The morning after you take BELSOMRA, your ability to drive safely and think clearly may be decreased. You may also have sleepiness during the day.
  - Do not take more BELSOMRA than prescribed.
  - Do not take BELSOMRA unless you are able to stay in bed a full night (at least 7 hours) before you must be active again.
  - Take BELSOMRA within 30 minutes of going to bed.

See "What are the possible side effects of BELSOMRA?" for more information about side effects.

What is BELSOMRA?

- BELSOMRA is a prescription medicine for adults who have trouble falling or staying asleep (insomnia).
- It is not known if BELSOMRA is safe and effective in children under the age of 18.

BELSOMRA is a federally controlled substance (C-IV) because it can be abused or cause dependence. Keep BELSOMRA in a safe place to prevent misuse and abuse. Selling or giving away BELSOMRA may harm others and is against the law. Tell your doctor if you have ever abused or have been dependent on alcohol, prescription medicines or street drugs.

Who should not take BELSOMRA?

Do not take BELSOMRA if you fall asleep often at unexpected times (narcolepsy).

What should I tell my doctor before taking BELSOMRA?

Before taking BELSOMRA, tell your doctor about all of your medical conditions, including if you:

- have a history of depression, mental illness, or suicidal thoughts
- have a history of drug or alcohol abuse or addiction
- have a history of a sudden onset of muscle weakness (cataplexy)
- have a history of falling asleep often at unexpected times (narcolepsy) or daytime sleepiness
- have lung problems or breathing problems
- have liver problems
- are pregnant or plan to become pregnant. It is not known if BELSOMRA can harm your unborn baby. Talk to your healthcare provider about the risk to your unborn baby if you take BELSOMRA during pregnancy.
- are breastfeeding or plan to breastfeed. BELSOMRA passes into your breast milk. Talk to your healthcare provider about the best way to feed your baby during treatment with BELSOMRA.

Tell your doctor about all the medicines you take, including prescription or over-the-counter medicines, vitamins, or herbal supplements. Medicines can interact with each other, sometimes causing serious side effects. Do not take BELSOMRA with other medicines that can make you sleepy unless your doctor tells you to.

Know the medicines you take. Keep a list of your medicines with you to show your doctor and pharmacist each time you get a new medicine.

How should I take BELSOMRA?

- Take BELSOMRA exactly as your doctor tells you to take it.
- Only take BELSOMRA 1 time each night, if needed, within 30 minutes of going to bed.
- Only take BELSOMRA when you can get a full night's sleep (at least 7 hours).
- Do not take BELSOMRA if you drank alcohol that evening or before bed.
- BELSOMRA may be taken with or without a meal. However, BELSOMRA may take longer to work if you take it with or right after meals.
- Call your doctor if your insomnia (sleep problem) worsens or is not better within 7 to 10 days. This may mean that there is another condition causing your sleep problem.
- If you take too much BELSOMRA, call your doctor right away or get emergency treatment.

What should I avoid while taking BELSOMRA?

- Do not drink alcohol while taking BELSOMRA. It can increase your chances of getting serious side effects.
- Do not drive, operate heavy machinery, do anything dangerous or do other activities that require clear thinking after taking BELSOMRA.
- You may still feel drowsy the next day after taking BELSOMRA. Do not drive or do other dangerous activities until you feel fully awake.

What are the possible side effects of BELSOMRA? See "What is the most important information I should know about BELSOMRA?"
BELSOMRA may cause serious side effects including:

- worsening depression and suicidal thoughts have happened during treatment with BELSOMRA. Call your healthcare provider right away if you have any worsening depression or thoughts of suicide or dying.
- complex sleep behaviors such as sleep-walking, sleep-driving, preparing and eating food, making phone calls, having sex or doing other activities while not fully awake that you may not remember the next morning. Call your healthcare provider right away if you experience a complex sleep behavior.
- temporary inability to move or talk (sleep paralysis) for up to several minutes while you are going to sleep or waking up.
- temporary weakness in your legs that can happen during the day or at night.

The most common side effects of BELSOMRA include drowsiness the next day after you take BELSOMRA.
The following additional side effects have been reported with BELSOMRA: abnormal dreams.

These are not all the possible side effects of BELSOMRA. For more information, ask your doctor or pharmacist.

Call your doctor for medical advice about side effects. You may report side effects to FDA at 1-800-FDA-1088.

How should I store BELSOMRA?

- Store BELSOMRA at room temperature between 68°F to 77°F (20°C to 25°C).
- Store in the original package until use, to protect from light and moisture.
- Keep BELSOMRA and all medicines out of reach of children.

General information about the safe and effective use of BELSOMRA.

Medicines are sometimes prescribed for purposes other than those listed in a Medication Guide. Do not use BELSOMRA for a condition for which it was not prescribed. Do not give BELSOMRA to other people, even if they have the same symptoms that you have. It may harm them.

This Medication Guide summarizes the most important information about BELSOMRA. You can ask your pharmacist or doctor for information about BELSOMRA that is written for health professionals.

For more information, go to www.BELSOMRA.com or call 1-800-622-4477.

What are the ingredients in BELSOMRA?

Active ingredient: Suvorexant

Inactive ingredients: Croscarmellose sodium, lactose monohydrate, magnesium stearate, microcrystalline cellulose, and polyvinylpyrrolidone/vinyl acetate copolymer (copovidone). The film coating contains: hypromellose, lactose monohydrate, titanium dioxide, and triacetin. The film coating for the 5 mg tablets also contains iron oxide black and iron oxide yellow, and the film coating for the 10 mg tablets also contains FD&C Blue #1/Brilliant Blue FCF Aluminum Lake and iron oxide yellow.

Distributed by: Merck Sharp & Dohme LLC
Rahway, NJ 07065, USA

For patent information: www.msd.com/research/patent

Copyright © 2014-2025 Merck & Co., Inc., Rahway, NJ, USA, and its affiliates.
All rights reserved.

usmg-mk4305-t-2503r007

This Medication Guide has been approved by the U.S. Food and Drug Administration.

Revised: 3/2025

PRINCIPAL DISPLAY PANEL - 5 mg Tablet Blister Card Case Carton

NDC 0006-0005-30

This package contains 30 Tablets in 3 Blister Cards.
Each Blister Card contains 10 Tablets.

Belsomra®
(suvorexant) tablets
CIV
5 mg

Dispense the accompanying Medication Guide to each patient.

Each tablet contains 5 mg suvorexant.

USUAL DOSAGE: See Package Insert.

Store at 20°C to 25°C (68°F to 77°F); excursions permitted to 15°C to 30°C (59°F to 86°F) [see USP Controlled
Room Temperature]. Store in the original package until use, to protect from light and moisture.

Selling or giving away Belsomra® may harm others and is against the law.

Rx only

PRINCIPAL DISPLAY PANEL - 10 mg Tablet Blister Card Case Carton

NDC 0006-0033-30

This package contains 30 Tablets in 3 Blister Cards.
Each Blister Card contains 10 Tablets.

Belsomra®
(suvorexant) tablets
CIV
10 mg

Dispense the accompanying Medication Guide to each patient.

Each tablet contains 10 mg suvorexant.

USUAL DOSAGE: See Package Insert.

Store at 20°C to 25°C (68°F to 77°F); excursions permitted to 15°C to 30°C (59°F to 86°F) [see USP Controlled
Room Temperature]. Store in the original package until use, to protect from light and moisture.

Selling or giving away Belsomra® may harm others and is against the law.

Rx only

PRINCIPAL DISPLAY PANEL - 15 mg Tablet Blister Card Case Carton

NDC 0006-0325-30

This package contains 30 Tablets in 3 Blister Cards.
Each Blister Card contains 10 Tablets.

Belsomra®
(suvorexant) tablets
CIV
15 mg

Dispense the accompanying Medication Guide to each patient.

Each tablet contains 15 mg suvorexant.

USUAL DOSAGE: See Package Insert.

Store at 20°C to 25°C (68°F to 77°F); excursions permitted to 15°C to 30°C (59°F to 86°F) [see USP Controlled
Room Temperature]. Store in the original package until use, to protect from light and moisture.

Selling or giving away Belsomra® may harm others and is against the law.

Rx only

PRINCIPAL DISPLAY PANEL - 20 mg Tablet Blister Card Case Carton

NDC 0006-0335-30

This package contains 30 Tablets in 3 Blister Cards.
Each Blister Card contains 10 Tablets.

Belsomra®
(suvorexant) tablets
CIV
20 mg

Dispense the accompanying Medication Guide to each patient.

Each tablet contains 20 mg suvorexant.

USUAL DOSAGE: See Package Insert.

Store at 20°C to 25°C (68°F to 77°F); excursions permitted to 15°C to 30°C (59°F to 86°F) [see USP Controlled
Room Temperature]. Store in the original package until use, to protect from light and moisture.

Selling or giving away Belsomra® may harm others and is against the law.

Rx only